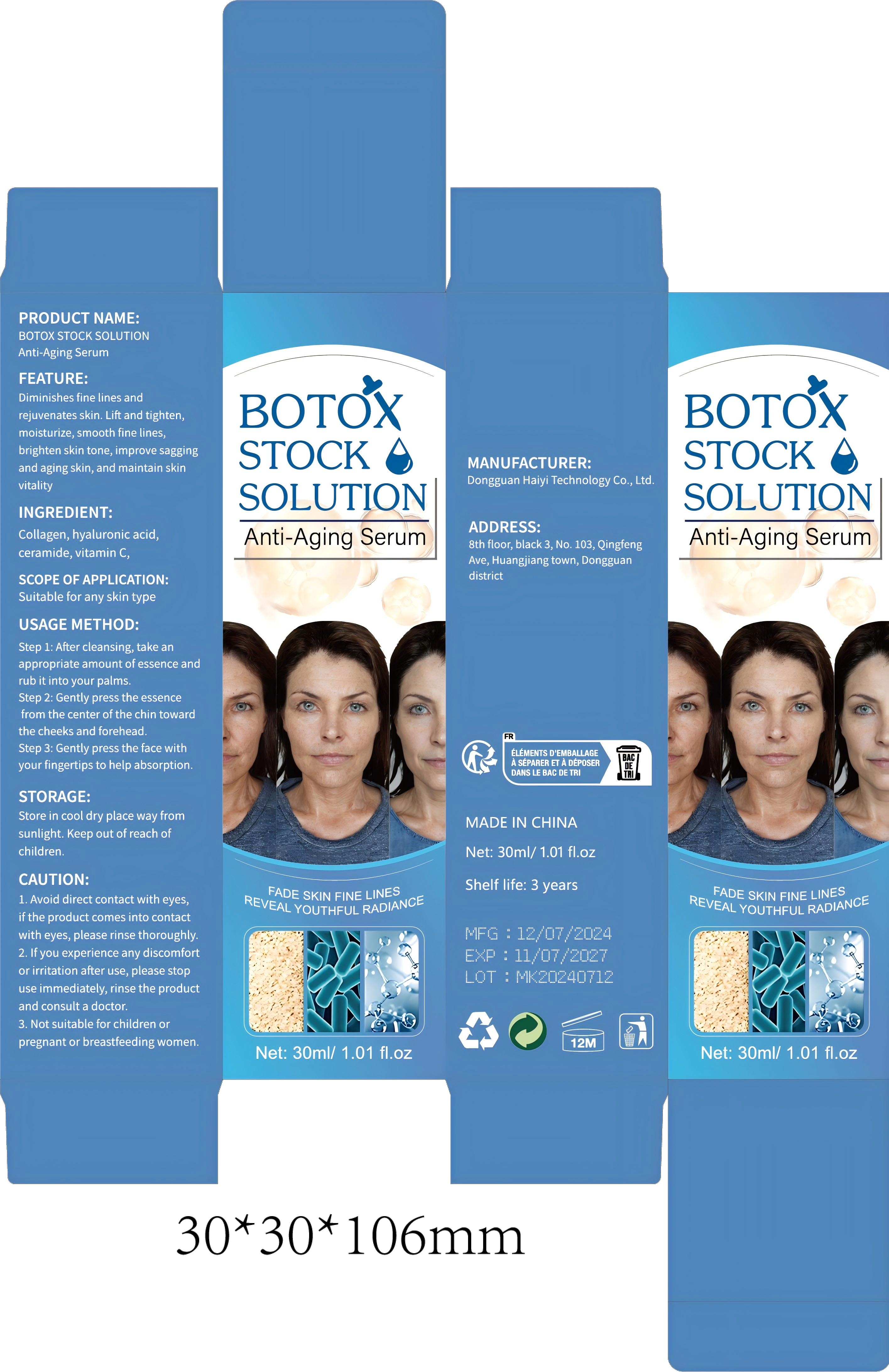 DRUG LABEL: Botulinum Toxin Solution Anti-Aging Serum
NDC: 84732-056 | Form: LIQUID
Manufacturer: Dongguan Haiyi Technology Co.,Ltd.
Category: otc | Type: HUMAN OTC DRUG LABEL
Date: 20241021

ACTIVE INGREDIENTS: PORK COLLAGEN 1 mg/30 mL
INACTIVE INGREDIENTS: HYALURONIC ACID; CERAMIDE NP; ASCORBIC ACID

Active ingredient

Collagen

Inactive ingredient

hyaluronic acid,ceramide, vitamin C,

Purpose section

Diminishes fine lines andrejuvenates skin. Lift and tighten,moisturize, smooth fine lines,brighten skin tone, improve saggingand aging skin, and maintain skin vitality

Warning

1. Avoid direct contact with eyes,if the product comes into contactwith eyes, please rinse thoroughly.

2. lf you experience any discomfortor irritation after use, please stopuse immediately, rinse the productand consult a doctor.

3. Not suitable for children orpregnant or breastfeeding women.

stop use

This product may cause allergic reactions in asmall number of people.
lf youexperience any discomfort,please stop using it immediately.

not use

Not suitable for use by children, pregnantor breast feeding people.

OUT OF CHILDREN

KEEP THE PRODUCT OUT OF REACH OF CHILDREN to

HOW TO USE

Step 1: After cleansing, take anappropriate amount of essence andrub it into your palms.

Step 2: Gently press the essencefrom the center of the chin towardthe cheeks and forehead.

Step 3: Gently press the face withyour fingertips to help absorption.

DOSAGE

take an appropriateamount,Use 2-3 times a week